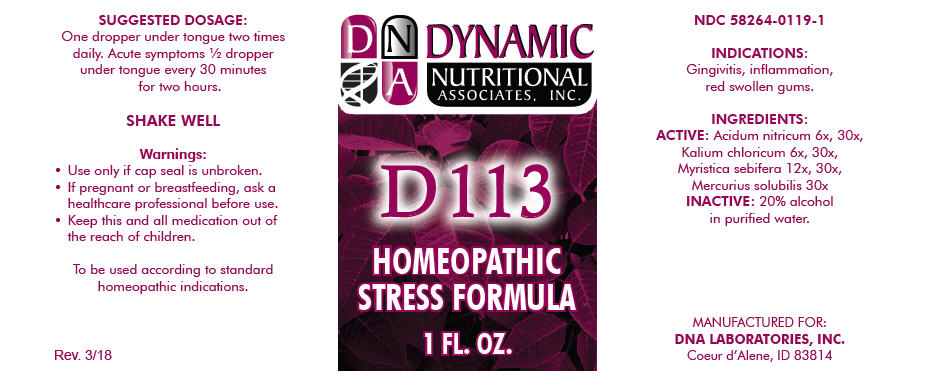 DRUG LABEL: D-113
NDC: 58264-0119 | Form: SOLUTION
Manufacturer: DNA Labs, Inc.
Category: homeopathic | Type: HUMAN OTC DRUG LABEL
Date: 20250113

ACTIVE INGREDIENTS: NITRIC ACID 6 [hp_X]/1 mL; POTASSIUM CHLORATE 6 [hp_X]/1 mL; VIROLA SEBIFERA RESIN 12 [hp_X]/1 mL; MERCURIUS SOLUBILIS 30 [hp_X]/1 mL
INACTIVE INGREDIENTS: ALCOHOL; WATER

D-113

NDC 58264-0119-1

INDICATIONS

PURPOSE

Gingivitis, inflammation, red swollen gums.

INGREDIENTS

ACTIVE

Acidum nitricum 6x, 30x, Kalium chloricum 6x, 30x, Myristica sebifera 12x, 30x, Mercurius solubilis 30x

INACTIVE

20% alcohol in purified water.

SUGGESTED DOSAGE

One dropper under tongue two times daily. Acute symptoms ½ dropper under tongue every 30 minutes for two hours.

STORAGE AND HANDLING

SHAKE WELL

Warnings

- Use only if cap seal is unbroken.

PREGNANCY OR BREAST FEEDING

- If pregnant or breastfeeding, ask a healthcare professional before use.

KEEP OUT OF REACH OF CHILDREN

- Keep this and all medication out of the reach of children.

To be used according to standard homeopathic indications.

PRINCIPAL DISPLAY PANEL - 1 FL. OZ. Bottle Label

DYNAMIC
NUTRITIONAL
ASSOCIATES, INC.

D 113

HOMEOPATHIC
STRESS FORMULA

1 FL. OZ.